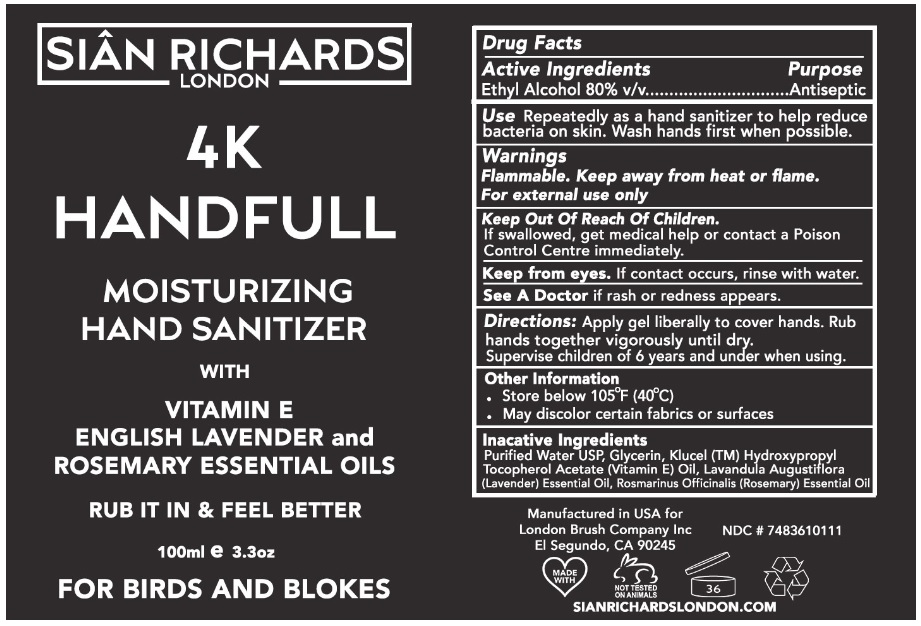 DRUG LABEL: 4K Handfull
NDC: 74836-101 | Form: GEL
Manufacturer: London Brush Company
Category: otc | Type: HUMAN OTC DRUG LABEL
Date: 20200623

ACTIVE INGREDIENTS: ALCOHOL 80 mL/100 mL
INACTIVE INGREDIENTS: WATER; GLYCERIN; HYDROXYPROPYL CELLULOSE (1600000 WAMW); .ALPHA.-TOCOPHEROL ACETATE; LAVENDER OIL; ROSEMARY OIL

4K HANDFULL MOISTURIZING HAND SANITIZER

Active Ingredients

Ethyl Alcohol 80% v/v

Purpose

Antiseptic

INDICATIONS AND USAGE

Use Repeatedly as a hand sanitizer to help reduce bacteria on skin. Wash hands first when possible.

Warnings

Flammable. Keep away from heat or flame.

For external use only

Keep from eyes. If contact occurs, rinse with water.

See A Doctor if rash or redness appears.

Keep Out Of Reach Of Children.

If swallowed, get medical help or contact a Poison Control Centre immediately.

DOSAGE AND ADMINISTRATION

Directions: Apply gel liberally to cover hands. Rub hands together vigorously until dry.

Supervise children of 6 years and under when using.

Other Information

• Store below 105°F (40°C)

• May discolor certain fabrics or surfaces

Inactive Ingredients

Purified Water USP, Glycerin, Klucel (TM) Hydroxypropyl, Tocopherol Acetate (Vitamin E) Oil, Lavandula Augustiflora (Lavender) Essential Oil, Rosemarinus Officinalis (Rosemary) Essential Oil

SIAN RICHARDS

LONDON

WITH

VITAMIN E

ENGLISH LAVENDER and ROSEMARY ESSENTIAL OILS

RUB IT IN & FEEL BETTER

FOR BIRDS AND BLOKES

Manufactured in USA for

London Brush Company Inc

EI Segundo, CA 90245

SIANRICHARDSLONDON.COM